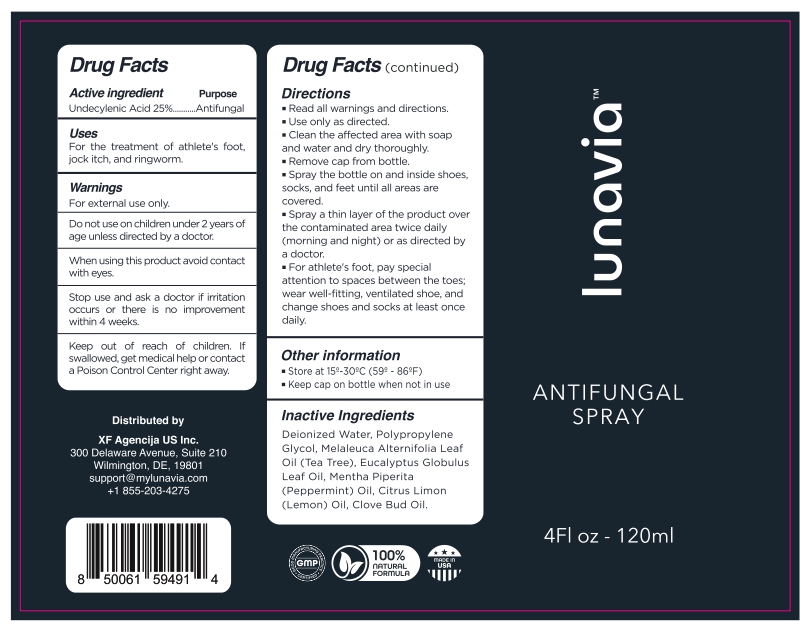 DRUG LABEL: Lunavia Antifungal
NDC: 85210-002 | Form: SPRAY
Manufacturer: XF Agencija Limited
Category: otc | Type: HUMAN OTC DRUG LABEL
Date: 20250613

ACTIVE INGREDIENTS: UNDECYLENIC ACID 25 g/100 mL
INACTIVE INGREDIENTS: WATER; PROPYLENE GLYCOL; TEA TREE OIL; EUCALYPTUS OIL; PEPPERMINT OIL; LEMON OIL, COLD PRESSED; CLOVE OIL

Lunavia Antifungal Spray

Active ingredient

Undecylenic Acid 25%

Purpose

Antifungal

Uses

For the treatment of athlete's foot, jock itch, and ringworm.

Warnings

For external use only.

Do not use on children under 2 years of age unless directed by a doctor.

When using this product avoid contact with eyes.

Stop use and ask a doctor if irritation occurs or there is no improvement within 4 weeks.

Keep out of reach of children. If swallowed, get medical help or contact a Poison Control Center right away.

Directions

■ Read all warnings and directions.

■ Use only as directed.
■ Clean the affected area with soap and water and dry thoroughly.

■ Remove cap from Bottle.

■ Spray the bottle on and inside shoes, socks, and feet until all areas are covered.

■ Spray a thin layer of the product over the contaminated area twice daily (morning and night) or as directed by a doctor.

■ For athlete's foot, pay special attention to spaces between the toes; wear well-fitting,ventilated shoe, and change shoes and socks at least once daily.

Other information

■ Store at 15°-30°C (59° - 86°F)
■ Keep cap on bottle when not in use

Inactive Ingredients

Deionized water, Polypropylene Glycol, Melaleuca Alternifolia Leaf Oil (Tea Tree), Eucalyptus Globulus Leaf oil, Mentha Piperita (Peppermint) Oil, Citrus Limon (Lemon) Oil, Clove Bud Oil.